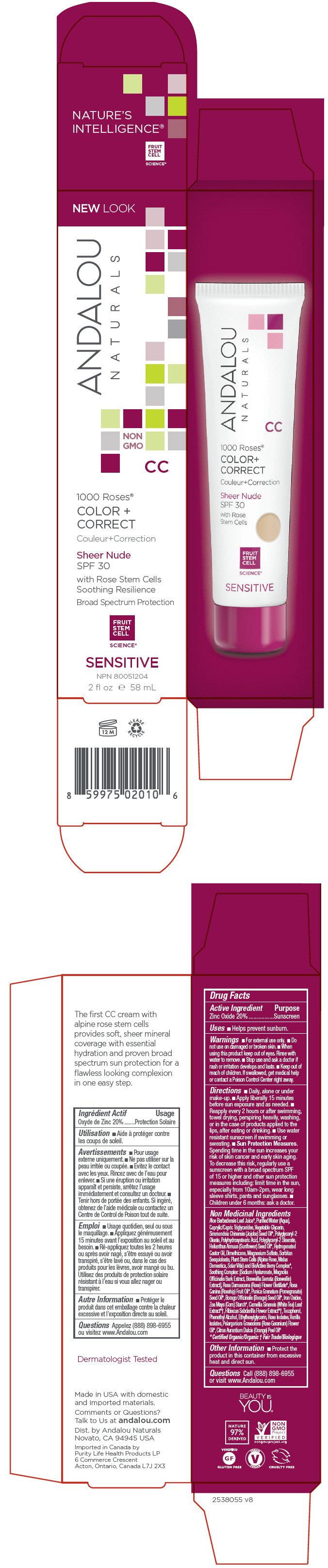 DRUG LABEL: 1000 Roses CC Color plus Correct Sheer Nude SPF 30
NDC: 55560-0105 | Form: LOTION
Manufacturer: Andalou naturals
Category: otc | Type: HUMAN OTC DRUG LABEL
Date: 20190712

ACTIVE INGREDIENTS: ZINC OXIDE 200 mg/1 mL
INACTIVE INGREDIENTS: ALOE VERA LEAF; WATER; MEDIUM-CHAIN TRIGLYCERIDES; GLYCERIN; JOJOBA OIL; POLYHYDROXYSTEARIC ACID (2300 MW); POLYGLYCERYL-2 STEARATE; SUNFLOWER OIL; HYDROGENATED CASTOR OIL; DIMETHICONE; MAGNESIUM SULFATE, UNSPECIFIED FORM; SORBITAN SESQUIOLEATE; ROSA RUGOSA FLOWER; APPLE; VITIS VINIFERA SEED; ACAI; ARONIA MELANOCARPA FRUIT JUICE; ARCTOSTAPHYLOS UVA-URSI LEAF; VACCINIUM MYRTILLUS ANTHOCYANOSIDES; EUROPEAN ELDERBERRY JUICE; LYCIUM BARBARUM FRUIT; ROSA CANINA FRUIT; HIPPOPHAE RHAMNOIDES FRUIT; HYALURONATE SODIUM; MAGNOLIA OFFICINALIS BARK; INDIAN FRANKINCENSE; ROSA X DAMASCENA FLOWER; ROSA MOSCHATA OIL; POMEGRANATE SEED OIL; BORAGE SEED OIL; FERRIC OXIDE YELLOW; STARCH, CORN; WHITE TEA; HIBISCUS SABDARIFFA FLOWER; TOCOPHEROL; PHENYLETHYL ALCOHOL; ETHYLHEXYLGLYCERIN; GERANIOL; VANILLIN; GERANIUM OIL, ALGERIAN TYPE; ORANGE OIL

1000 Roses® CC Color + Correct Sheer Nude SPF 30

Drug Facts

Active Ingredient

Zinc Oxide 20%

Purpose

Sunscreen

Uses

- Helps prevent sunburn.

Warnings

- For external use only.

- Do not use on damaged or broken skin.

- When using this product keep out of eyes. Rinse with water to remove.

- Stop use and ask a doctor if rash or irritation develops and lasts.

- Keep out of reach of children. If swallowed, get medical help or contact a Poison Control Center right away.

Directions

- Daily, alone or under make-up.
- Apply liberally 15 minutes before sun exposure and as needed.
- Reapply every 2 hours or after swimming, towel drying, perspiring heavily, washing, or in the case of products applied to the lips, after eating or drinking.
- Use water resistant sunscreen if swimming or sweating.
- Sun Protection Measures. Spending time in the sun increases your risk of skin cancer and early skin aging. To decrease this risk, regularly use a sunscreen with a broad spectrum SPF of 15 or higher and other sun protection measures including: limit time in the sun, especially from 10am-2pm, wear long sleeve shirts, pants and sunglasses.
- Children under 6 months: ask a doctor.

Non Medicinal Ingredients

Aloe Barbadensis Leaf Juice [Certified Organic/Organic] , Purified Water (Aqua), Caprylic/Capric Triglycerides, Vegetable Glycerin, Simmondsia Chinensis (Jojoba) Seed Oil, Polyglyceryl-2 Oleate, Polyhydroxystearic Acid, Polyglyceryl-2 Stearate, Helianthus Annuus (Sunflower) Seed Oil, Hydrogenated Castor Oil, Dimethicone, Magnesium Sulfate, Sorbitan Sesquioleate, Plant Stem Cells (Alpine Rose, Malus Domestica, Solar Vitis) and BioActive Berry Complex, Soothing Complex: [Sodium Hyaluronate, Magnolia Officinalis Bark Extract, Boswellia Serrata (Boswellin) Extract], Rosa Damascena (Rose) Flower Distillate, Rosa Canina (Rosehip) Fruit Oil, Punica Granatum (Pomegranate) Seed Oil, Borago Officinalis (Borage) Seed Oil, Iron Oxides, Zea Mays (Corn) Starch, Camellia Sinensis (White Tea) Leaf Extract [Fair Trade/Biologique] , Hibiscus Sabdariffa Flower Extract, Tocopherol, Phenethyl Alcohol, Ethylhexylglycerin, Rose Isolates, Vanilla Isolates, Pelargonium Graveolens (Rose Geranium) Flower Oil, Citrus Aurantium Dulcis (Orange) Peel Oil

Other Information

- Protect the product in this container from excessive heat and direct sun.

Questions

Call (888) 898-6955 or visit www.Andalou.com

Dist. by Andalou Naturals
Novato, CA 94945 USA

PRINCIPAL DISPLAY PANEL - 58 mL Tube Carton

NEW LOOK

ANDALOU
NATURALS

NON
GMO

CC

1000 Roses®

COLOR +
CORRECT

Sheer Nude
SPF 30

with Rose Stem Cells
Soothing Resilience

Broad Spectrum Protection

FRUIT
STEM
CELL
SCIENCE®

SENSITIVE

NPN 80051204

2 fl oz e 58 mL